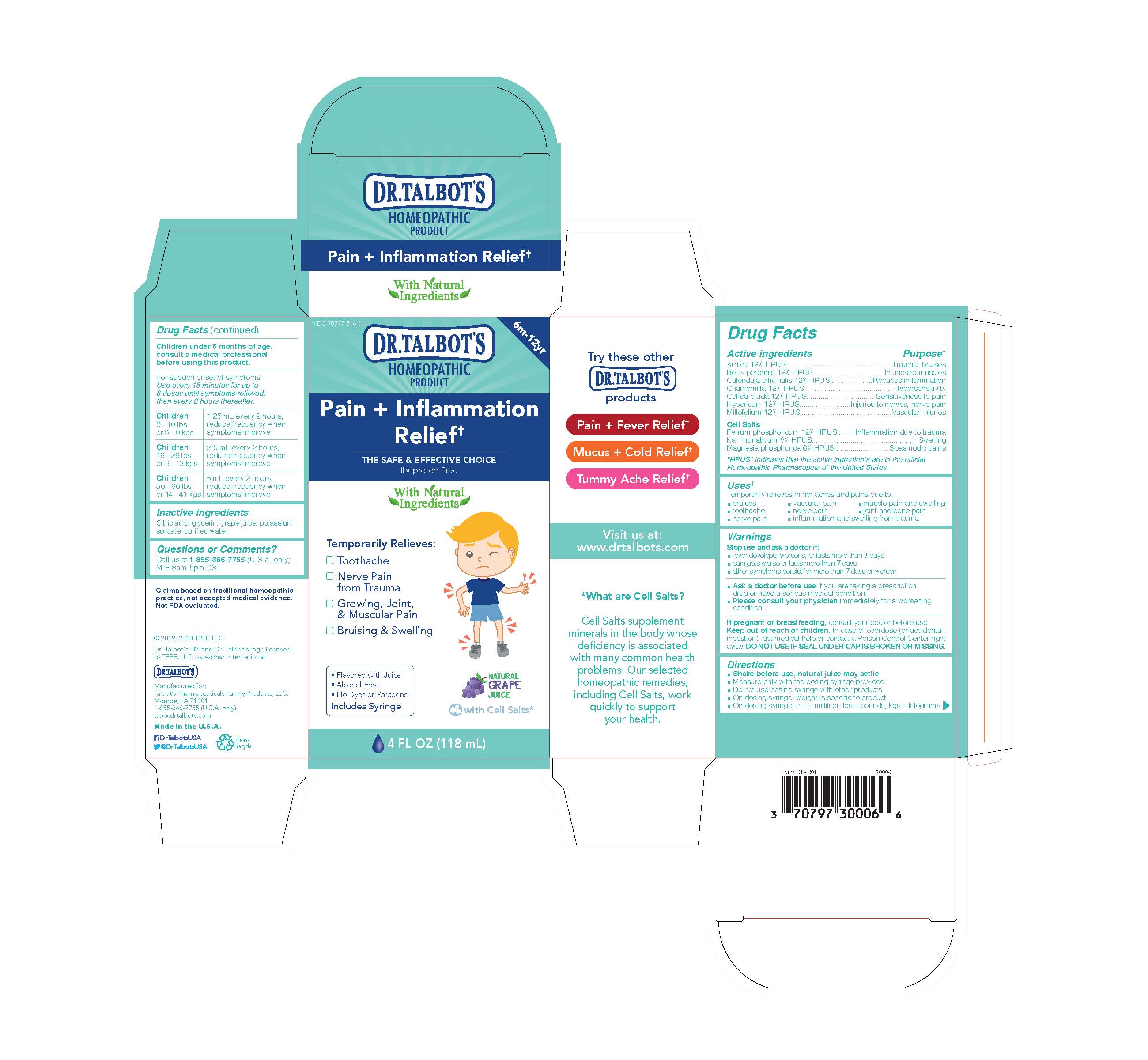 DRUG LABEL: Dr. Talbots Pain Inflammation Relief
NDC: 70797-316 | Form: LIQUID
Manufacturer: Talbot's Pharmaceuticals Family Products, LLC.
Category: homeopathic | Type: HUMAN OTC DRUG LABEL
Date: 20211005

ACTIVE INGREDIENTS: ARABICA COFFEE BEAN 12 [hp_X]/118 mL; MAGNESIUM PHOSPHATE, DIBASIC 6 [hp_X]/118 mL; ACHILLEA MILLEFOLIUM 12 [hp_X]/118 mL; ARNICA MONTANA 12 [hp_X]/118 mL; FERROSOFERRIC PHOSPHATE 12 [hp_X]/118 mL; HYPERICUM PERFORATUM 12 [hp_X]/118 mL; BELLIS PERENNIS 12 [hp_X]/118 mL; CALENDULA OFFICINALIS FLOWERING TOP 12 [hp_X]/118 mL; MATRICARIA CHAMOMILLA 12 [hp_X]/118 mL; POTASSIUM CHLORIDE 6 [hp_X]/118 mL
INACTIVE INGREDIENTS: CITRIC ACID MONOHYDRATE; GLYCERIN; CONCORD GRAPE JUICE; POTASSIUM SORBATE; WATER

Active Ingredients

Arnica 12X HPUS
Bellis perennis 12X HPUS
Calendula Officinalis 12X HPUS
Chamomilla 12X HPUS

Coffea cruda 12X HPUS
Hypericum 12X HPUS
Millefolium 12X HPUS
Cell Salts
Ferrum phosphoricum 12X HPUS
Kali muriaticum 6X HPUS

Magnesia phosphorica 6XHPUS

Uses

Temporarily relieves minor aches and pains due to:

- bruises
- toothache
- nerve pain
- vascular pain
- nerve pain
- inflammation and swelling from trauma
- muscle pain and swelling
- joint and bone pain

Warnings

Stop use and ask doctor if:

- fever develops, worsens, or lasts more than 3 days
- pain gets worse or lasts more than 7 days
- other symptoms persist for more than 7 days or worsen
- Ask a doctor before use if you are taking a prescription drug or have a serious medical condition.
- Please consult your physician immediately for a worsening condition.

Pregnancy or breastfeeding

If pregnant or breastfeeding, consult your doctor before use.

Keep out of reach of children. In case of overdoes (or accidental ingestion), get medical help or contact a Poison Control Center right away. DO NOT USE IF SEAL UNDER CAP IS BROKEN OR MISSING.

Directions

- Shake before use, natural juice may settle
- Measure only with the dosing syringe provided
- Do not use dosing syringe with other products
- On dosing syringe, weight is specific to product
- On dosing syringe, ml = milliliter, lbs = pounds, kgs = kilograms

Children under 6 months of age, consult a medical professional before using this product.

For sudden onset of symptoms: Use every 15 minutes for up to 8 doses until symptoms relieved, then every 2 hours thereafter.

Children 6 - 18 lbs or 3 - 8 kgs

1.25 ml every 2 hours, reduce frequency when symptoms improve

Children 19 - 29 lbs or 9 - 13 kgs

2.5 ml every 2 hours, reduce frequency when symptoms improve

Children 30 - 90 lbs or 14 - 41 kgs

5 ml every 2 hours, reduce frequency when symptoms improve

Inactive Ingredients

Citric acid, glycerin, grape juice, potassium sorbate, purified water

Questions

Questions or Comments?

Call us at 1-800-588-6227

M-F 8am-5pm CST

Purpose

Trauma, bruises
Injuries to muscles

Reduces inflammation
Hypersensitivity

Sensitiveness to pain
Injuries to nerves, nerve pain
Vascular injuries
Inflammation due to trauma
Swelling

Spasmodic pains